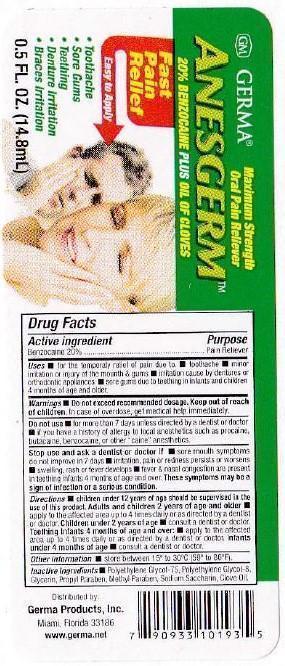 DRUG LABEL: Anesgerm
NDC: 10095-001 | Form: GEL
Manufacturer: World Perfumes, Inc
Category: otc | Type: HUMAN OTC DRUG LABEL
Date: 20150508

ACTIVE INGREDIENTS: BENZOCAINE 0.2 g/100 g
INACTIVE INGREDIENTS: ALCOHOL; CLOVE OIL; GLYCERIN; METHYLPARABEN; POLYETHYLENE GLYCOL 1000; PROPYLENE GLYCOL; SACCHARIN SODIUM

Active Ingredient Purpose

Benzocaine 20% .................................... Pain Reliever

Uses

for the temporary relief of pain due to:

- toothache
- minor irritation or injury of the mouth and gums
- infection cause by dentures or orthodontic appliances
- sore gums due to teething in infants and children 4 months of age and older

Keep out of reach of children. In case of overdose, get medical help immediately.

Directions

children under 12 years of age should be supervised in the use of this product. Adults and children 12 years of age and older:

- apply to the affected area up to 4 times a day or as directed by a dentist or doctor

Children under 2 years of age:

- consult a dentist or doctor

Teething Infants 4 months of age and over:

- apply to the affected area up to 4 times daily or as directed by a dentist or doctor

Infants under 4 months of age:

- consult a dentist or doctor

INDICATIONS AND USAGE

GERMA

Anesterm

Maximum Strength Oral Pain Reliever

20% Benzocaine PLUS Oil of Cloves

Fast Pain Relief

Easy To Apply

- Toothache
- Sore Gums
- Teething
- Denture Irritation
- Braces Irritation

Warnings

Do not exceed recommended dosage.

Do not use

- for more than 7 days unless directed by a dentist or doctor
- if you have a history of allergy to local anesthetics such as procaine, butacaine, benzocaine, or other "caine" anesthetics

Stop use and ask a doctor if

- sore mouth symptoms do not improve in 7 days
- infection, pain, or redness persists or worsens
- swelling, rash or fever develops
- fever & nasal congestion are present in teething infants 4 months of age and over

These symptoms may be a sign of infection or a serious condition.

Inactive Ingredients

polyethylene glycol-75, polyethylene glycol-8, glycerin, propyl paraben, methyl paraben, sodium saccharin, clove oil